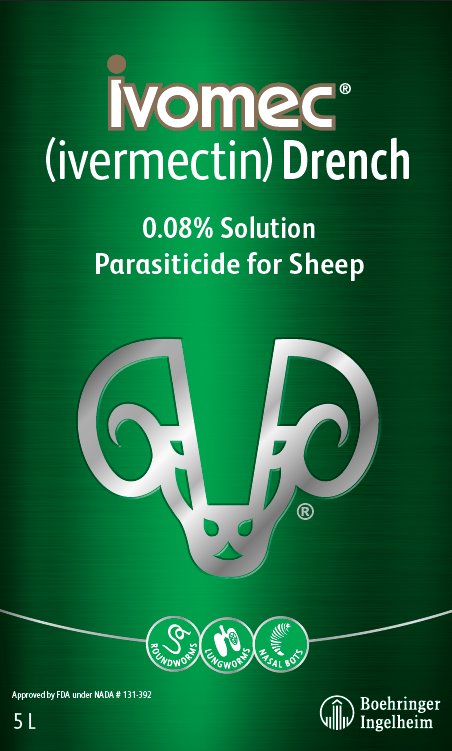 DRUG LABEL: IVOMEC
NDC: 0010-4745 | Form: SOLUTION
Manufacturer: Boehringer Ingelheim Animal Health USA Inc.
Category: animal | Type: OTC ANIMAL DRUG LABEL
Date: 20251031

ACTIVE INGREDIENTS: ivermectin 0.0008 mg/1 L

Ivomec®
(ivermectin) Drench

0.08% Solution

Parasiticide for Sheep

Approved by FDA under NADA # 131-392

Consult your veterinarian for assistance in the diagnosis, treatment, and control of parasitism.

FOR ORAL USE IN SHEEP ONLY. NOT FOR HUMAN USE.

PRODUCT DESCRIPTION:

IVOMEC Drench is a ready-to-use, free-flowing solution of ivermectin for use in sheep. It is formulated to deliver the recommended dose rate of 0.2 mg ivermectin per 1 kg body weight given orally at a volume of 3.0 mL per 26 lb body weight.

INDICATIONS:

IVOMEC Drench provides treatment and control of adult and fourth-stage larvae of the following parasites: Gastrointestinal Roundworms - Haemonchus contortus, Ostertagia circumcincta, Trichostrongylus axei, T. colubriformis, Cooperia curticei, Nematodirus spathiger, N. battus, and Oesophagostomum columbianum; Lungworms - Dictyocaulus filaria; and all the larval stages of Nasal Bot - Oestrus ovis. It also provides treatment and control of adult forms only of the following Gastrointestinal Roundworms - Haemonchus placei, Cooperia oncophora, Strongyloides papillosus, Oesophagostomum venulosum, Trichuris ovis, and Chabertia ovina.

DOSAGE AND ADMINISTRATION:

IVOMEC Drench may be used in any standard drenching equipment or in any equipment which provides a consistent dose volume. IVOMEC Drench is administered orally at a dose of 3.0 mL (2.4 mg ivermectin) per 26 lb body weight or 200 mcg ivermectin per kilogram of body weight.

Coughing may be observed in some animals during and for several minutes following drenching.

Do not underdose. Ensure each animal receives a complete dose based on a current body weight. Underdosing may result in ineffective treatment, and encourage the development of parasite resistance.

RESIDUE WARNING:

Do not treat sheep within 11 days of slaughter.

The Safety Data Sheet (SDS) contains more detailed occupational safety information. To report adverse effects in users, to obtain an SDS, or for assistance call 1-888-637-4251.

PRECAUTIONS:

IVOMEC Drench has been formulated specifically for use in sheep only. This product should not be used in other animal species as severe adverse reactions, including fatalities in dogs, may result.

OTHER WARNINGS:

Parasite resistance may develop to any dewormer, and has been reported for most classes of dewormers.

Treatment with a dewormer used in conjunction with parasite management practices appropriate to the geographic area and the animal(s) to be treated may slow the development of parasite resistance.

Fecal examinations or other diagnostic tests and parasite management history should be used to determine if the product is appropriate for the flock, prior to the use of any dewormer. Following the use of any dewormer, effectiveness of treatment should be monitored (for example, with the use of a fecal egg count reduction test or another appropriate method).

A decrease in a drug's effectiveness over time as calculated by fecal egg count reduction tests may indicate the development of resistance to the dewormer administered. Your parasite management plan should be adjusted accordingly based on regular monitoring.

Keep this and all drugs out of reach of children.

Refrain from smoking and eating when handling. Avoid contact with eyes. Immediately wash hands and any spills on the skin with plenty of soap and water following use.

Restricted Drug (California) - Use only as directed.

ENVIRONMENTAL SAFETY:

Studies indicate that when ivermectin comes in contact with the soil, it readily and tightly binds to the soil and becomes inactive over time. Free ivermectin may adversely affect fish and certain water-borne organisms on which they feed. Do not permit water runoff from feedlots to enter lakes, streams or ground water. Do not contaminate water by direct application or by the improper disposal of drug containers. Spills should be contained and soaked up with absorbent towels or into loose soil. Gloves should be worn to prevent skin exposure. All the collected materials (contaminated towels and soil), as well as all empty drug containers should be placed in an impervious film (plastic) bag and disposed of by incineration or in an approved landfill.

STORAGE INFORMATION:

Store at 68° – 77° F (20° – 25° C). Excursions between 59° – 86° F (15° – 30° C) are permitted.

IVOMEC® and Sheep Head Logo are registered
trademarks of Boehringer Ingelheim Animal Health USA Inc.

©2024 Boehringer Ingelheim Animal Health USA Inc. All rights reserved.

Marketed by:

Boehringer Ingelheim Animal Health USA Inc.

Duluth, GA 30096

Origin China

1030-2533-05 / Rev 10/2024